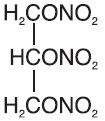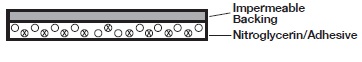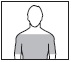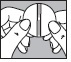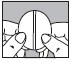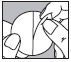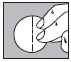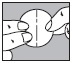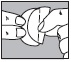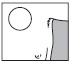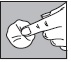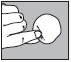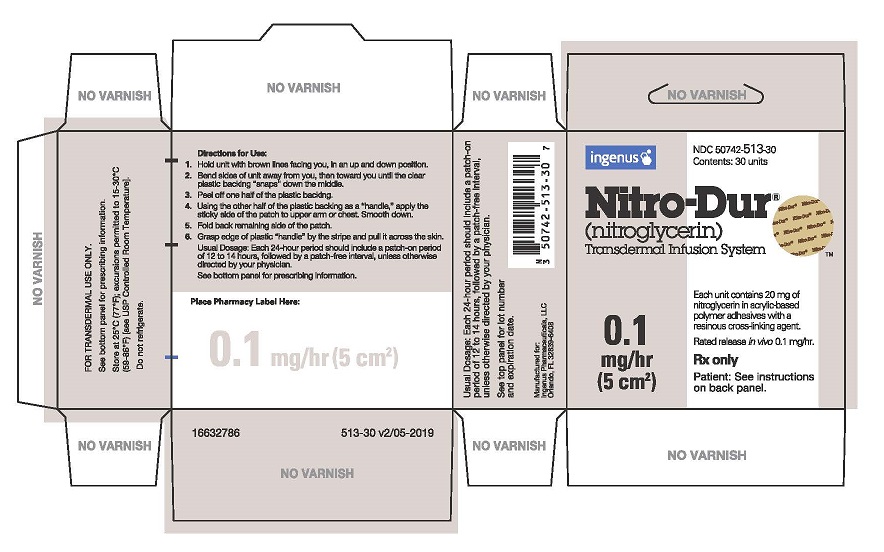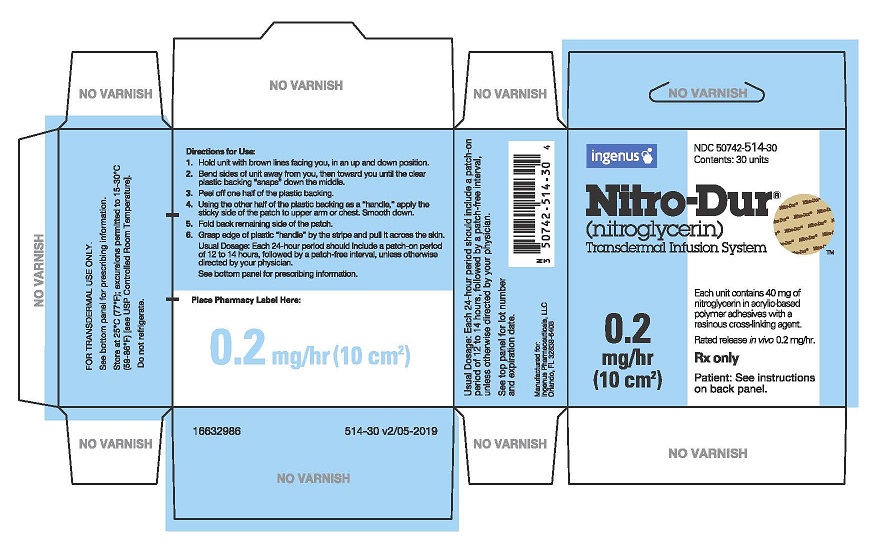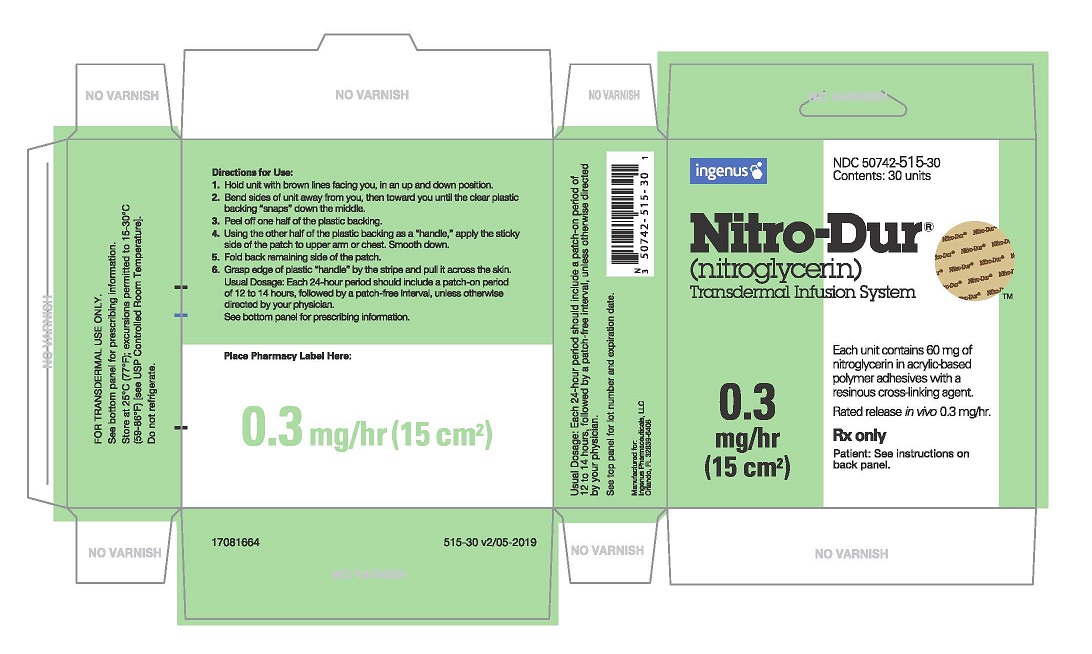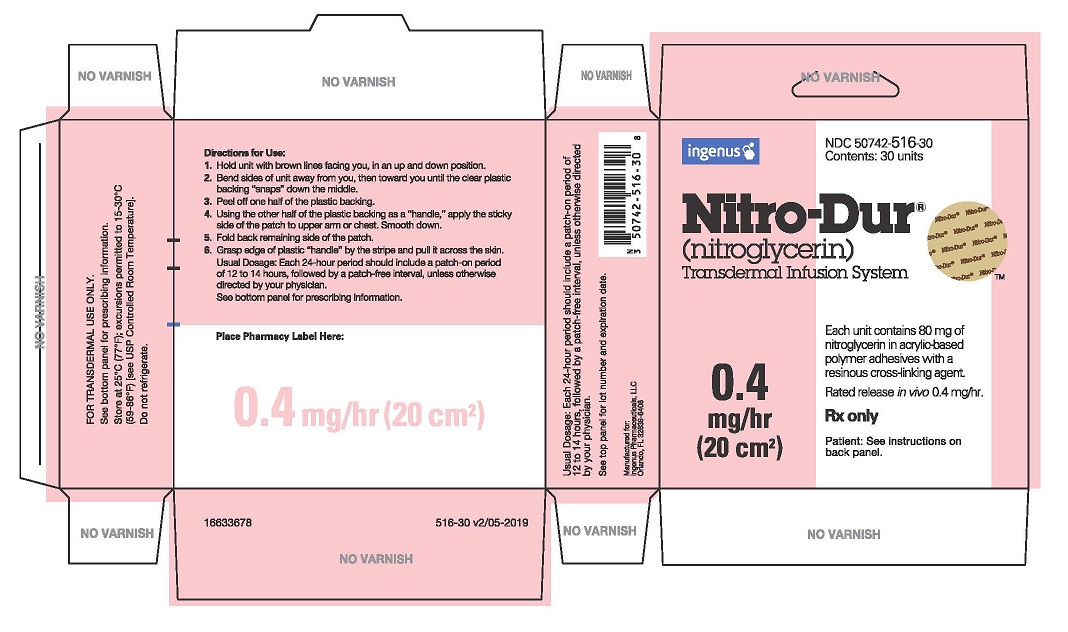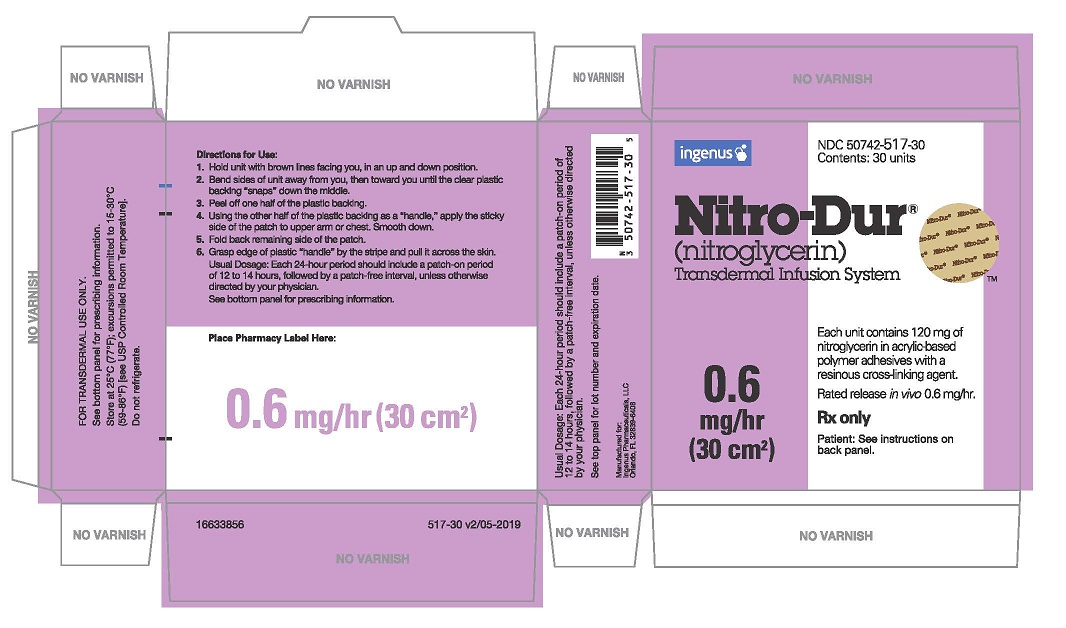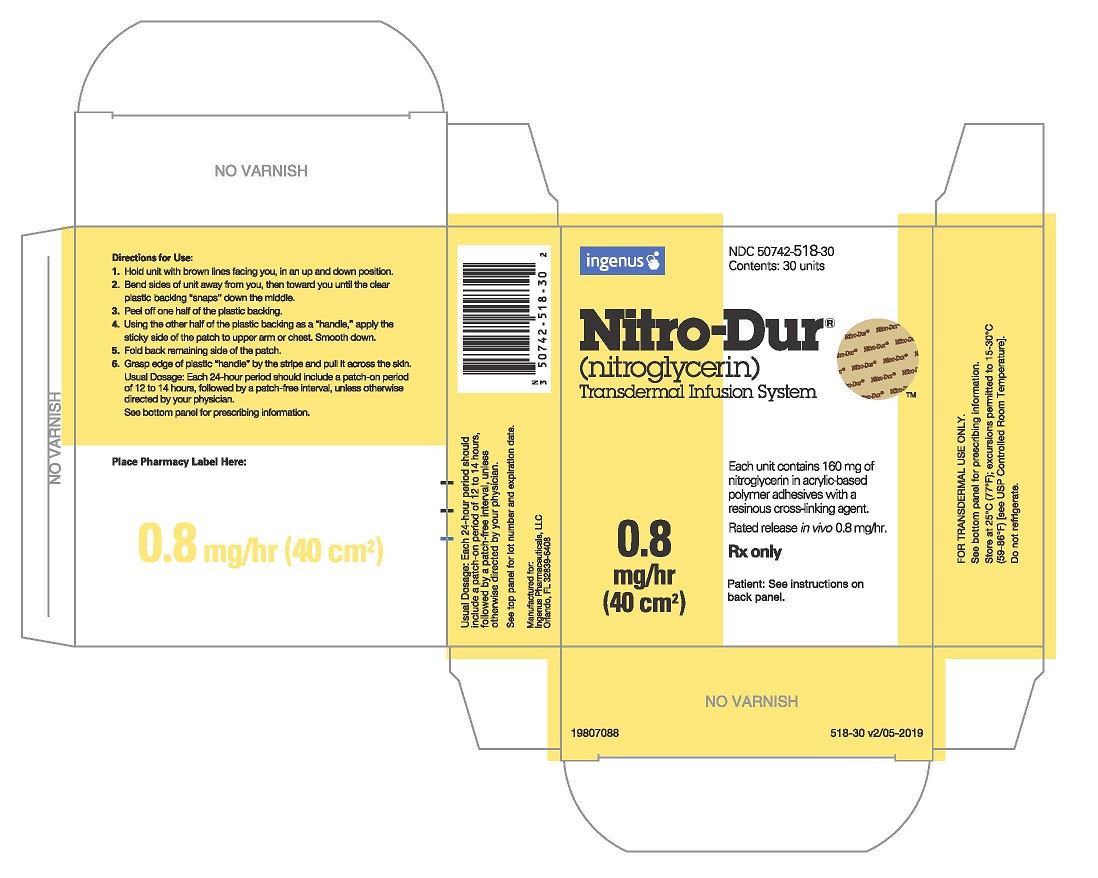 DRUG LABEL: NITRO-DUR
NDC: 50742-513 | Form: PATCH
Manufacturer: Ingenus Pharmaceuticals, LLC
Category: prescription | Type: HUMAN PRESCRIPTION DRUG LABEL
Date: 20230530

ACTIVE INGREDIENTS: NITROGLYCERIN 20 mg/1 1

NITRO-DUR®
(nitroglycerin)
Transdermal Infusion System

DESCRIPTION

Nitroglycerin is 1,2,3-propanetriol trinitrate, an organic nitrate whose structural formula is:

and whose molecular weight is 227.09. The organic nitrates are vasodilators, active on both arteries and veins.

The NITRO-DUR® (nitroglycerin) Transdermal Infusion System is a flat unit designed to provide continuous controlled release of nitroglycerin through intact skin. The rate of release of nitroglycerin is linearly dependent upon the area of the applied system; each cm^2 of applied system delivers approximately 0.02 mg of nitroglycerin per hour. Thus, the 5-,10-, 15-, 20-, 30-, and 40-cm2 systems deliver approximately 0.1, 0.2, 0.3, 0.4, 0.6, and 0.8 mg of nitroglycerin per hour, respectively.

The remainder of the nitroglycerin in each system serves as a reservoir and is not delivered in normal use. After 12 hours, for example, each system has delivered approximately 6% of its original content of nitroglycerin.

The NITRO-DUR transdermal system contains nitroglycerin in acrylic-based polymer adhesives with a resinous cross-linking agent to provide a continuous source of active ingredient. Each unit is sealed in a paper polyethylene-foil pouch.
Cross section of the system.

CLINICAL PHARMACOLOGY

The principal pharmacological action of nitroglycerin is relaxation of vascular smooth muscle and consequent dilatation of peripheral arteries and veins, especially the latter. Dilatation of the veins promotes peripheral pooling of blood and decreases venous return to the heart, thereby reducing left ventricular end-diastolic pressure and pulmonary capillary wedge pressure (preload). Arteriolar relaxation reduces systemic vascular resistance, systolic arterial pressure, and mean arterial pressure (afterload). Dilatation of the coronary arteries also occurs. The relative importance of preload reduction, afterload reduction, and coronary dilatation remains undefined.

Dosing regimens for most chronically used drugs are designed to provide plasma concentrations that are continuously greater than a minimally effective concentration. This strategy is inappropriate for organic nitrates. Several well-controlled clinical trials have used exercise testing to assess the antianginal efficacy of continuously delivered nitrates. In the large majority of these trials, active agents were indistinguishable from placebo after 24 hours (or less) of continuous therapy. Attempts to overcome nitrate tolerance by dose escalation, even to doses far in excess of those used acutely, have consistently failed. Only after nitrates have been absent from the body for several hours has their antianginal efficacy been restored.

Pharmacokinetics

The volume of distribution of nitroglycerin is about 3 L/kg, and nitroglycerin is cleared from this volume at extremely rapid rates, with a resulting serum half-life of about 3 minutes. The observed clearance rates (close to 1 L/kg/min) greatly exceed hepatic blood flow; known sites of extrahepatic metabolism include red blood cells and vascular walls.

The first products in the metabolism of nitroglycerin are inorganic nitrate and the 1,2- and 1,3-dinitroglycerols. The dinitrates are less effective vasodilators than nitroglycerin, but they are longerlived in the serum, and their net contribution to the overall effect of chronic nitroglycerin regimens is not known. The dinitrates are further metabolized to (nonvasoactive) mononitrates and, ultimately, to glycerol and carbon dioxide.

To avoid development of tolerance to nitroglycerin, drug-free intervals of 10 to 12 hours are known to be sufficient; shorter intervals have not been well studied. In one well-controlled clinical trial, subjects receiving nitroglycerin appeared to exhibit a rebound or withdrawal effect, so that their exercise tolerance at the end of the daily drug-free interval was less than that exhibited by the parallel group receiving placebo.

In healthy volunteers, steady-state plasma concentrations of nitroglycerin are reached by about 2 hours after application of a patch and are maintained for the duration of wearing the system (observations have been limited to 24 hours). Upon removal of the patch, the plasma concentration declines with a half-life of about an hour.

Clinical Trials

Regimens in which nitroglycerin patches were worn for 12 hours daily have been studied in wellcontrolled trials up to 4 weeks in duration. Starting about 2 hours after application and continuing until 10 to 12 hours after application, patches that deliver at least 0.4 mg of nitroglycerin per hour have consistently demonstrated greater antianginal activity than placebo. Lower-dose patches have not been as well studied, but in one large, well-controlled trial in which higher-dose patches were also studied, patches delivering 0.2 mg/hr had significantly less antianginal activity than placebo.

It is reasonable to believe that the rate of nitroglycerin absorption from patches may vary with the site of application, but this relationship has not been adequately studied.

INDICATIONS AND USAGE

Transdermal nitroglycerin is indicated for the prevention of angina pectoris due to coronary artery disease. The onset of action of transdermal nitroglycerin is not sufficiently rapid for this product to be useful in aborting an acute attack.

CONTRAINDICATIONS

Nitroglycerin is contraindicated in patients who are allergic to it. Allergy to the adhesives used in nitroglycerin patches has also been reported, and it similarly constitutes a contraindication to the use of this product.

Do not use NITRO-DUR in patients who are taking phosphodiesterase inhibitors (such as sildenafil, tadalafil, or vardenafil) for erectile dysfunction or pulmonary arterial hypertension. Concomitant use can cause severe drops in blood pressure.
Do not use NITRO-DUR in patients who are taking the soluble guanylate cyclase stimulator riociguat. Concomitant use can cause hypotension.

WARNINGS

Amplification of the vasodilatory effects of the NITRO-DUR patch by phosphodiesterase inhibitors, eg, sildenafil can result in severe hypotension. The time course and dose dependence of this inter action have not been studied. Appropriate supportive care has not been studied, but it seems reasonable to treat this as a nitrate overdose, with elevation of the extremities and with central volume expansion.

The benefits of transdermal nitroglycerin in patients with acute myocardial infarction or congestive heart failure have not been established. If one elects to use nitroglycerin in these conditions, careful clinical or hemodynamic monitoring must be used to avoid the hazards of hypotension and tachycardia.

A cardioverter/defibrillator should not be discharged through a paddle electrode that overlies a NITRO-DUR patch. The arcing that may be seen in this situation is harmless in itself, but it may be associated with local current concentration that can cause damage to the paddles and burns to the patient.

PRECAUTIONS

General:

Severe hypotension, particularly with upright posture, may occur with even small doses of nitroglycerin, particularly in the elderly. The NITRO-DUR Transdermal Infusion System should therefore be used with caution in elderly patients who may be volume-depleted, are on multiple medications, or who, for whatever reason, are already hypotensive. Hypotension induced by nitroglycerin may be accompanied by paradoxical bradycardia and increased angina pectoris.

Elderly patients may be more susceptible to hypotension and may be at greater risk of falling at the therapeutic doses of nitroglycerin.

Nitrate therapy may aggravate the angina caused by hypertrophic cardiomyopathy, particularly in the elderly.

In industrial workers who have had long-term exposure to unknown (presumably high) doses of organic nitrates, tolerance clearly occurs. Chest pain, acute myocardial infarction, and even sudden death have occurred during temporary withdrawal of nitrates from these workers, demonstrating the existence of true physical dependence.

Several clinical trials in patients with angina pectoris have evaluated nitroglycerin regimens which incorporated a 10- to 12-hour, nitrate-free interval. In some of these trials, an increase in the frequency of anginal attacks during the nitrate-free interval was observed in a small number of patients. In one trial, patients had decreased exercise tolerance at the end of the nitrate-free interval. Hemodynamic rebound has been observed only rarely; on the other hand, few studies were so designed that rebound, if it had occurred, would have been detected. The importance of these observations to the routine, clinical use of transdermal nitroglycerin is unknown.

Information for Patients:

Daily headaches sometimes accompany treatment with nitroglycerin. In patients who get these headaches, the headaches may be a marker of the activity of the drug. Patients should resist the temptation to avoid headaches by altering the schedule of their treatment with nitroglycerin, since loss of headache may be associated with simultaneous loss of antianginal efficacy.

Treatment with nitroglycerin may be associated with lightheadedness on standing, especially just after rising from a recumbent or seated position. This effect may be more frequent in patients who have also consumed alcohol.

After normal use, there is enough residual nitroglycerin in discarded patches that they are a potential hazard to children and pets.

A patient leaflet is supplied with the systems.

Drug Interactions:

The vasodilating effects of nitroglycerin may be additive with those of other vasodilators. Alcohol, in particular, has been found to exhibit additive effects of this variety.

Concomitant use of NITRO-DUR with phosphodiesterase inhibitors in any form is contraindicated (see CONTRAINDICATIONS).

Concomitant use of NITRO-DUR with riociguat, a soluble guanylate cyclase stimulator, is contraindicated (see CONTRAINDICATIONS).

Carcinogenesis, Mutagenesis, Impairment of Fertility:

Animal carcinogenesis studies with topically applied nitroglycerin have not been performed.

Rats receiving up to 434 mg/kg/day of dietary nitroglycerin for 2 years developed dose-related fibrotic and neoplastic changes in liver, including carcinomas, and interstitial cell tumors in testes. At high dose, the incidences of hepatocellular carcinomas in both sexes were 52% vs 0% in controls, and incidences of testicular tumors were 52% vs 8% in controls. Lifetime dietary administration of up to 1058 mg/kg/day of nitroglycerin was not tumorigenic in mice.

Nitroglycerin was weakly mutagenic in Ames tests performed in two different laboratories. Nevertheless, there was no evidence of mutagenicity in an in vivo dominant lethal assay with male rats treated with doses up to about 363 mg/kg/day, po, or in in vitro cytogenetic tests in rat and dog tissues.

In a three-generation reproduction study, rats received dietary nitroglycerin at doses up to about 434 mg/kg/day for 6 months prior to mating of the F0 generation with treatment continuing through successive F1 and F2 generations. The high dose was associated with decreased feed intake and body weight gain in both sexes at all matings. No specific effect on the fertility of the F0 generation was seen. Infertility noted in subsequent generations, however, was attributed to increased interstitial cell tissue and aspermatogenesis in the high-dose males. In this three-generation study there was no clear evidence of teratogenicity.

Pregnancy:

Pregnancy Category C:

Animal teratology studies have not been conducted with nitroglycerin transdermal systems. Teratology studies in rats and rabbits, however, were conducted with topically applied nitroglycerin ointment at doses up to 80 mg/kg/day and 240 mg/kg/day, respectively. No toxic effects on dams or fetuses were seen at any dose tested. There are no adequate and wellcontrolled studies in pregnant women. Nitroglycerin should be given to a pregnant woman only if clearly needed.

Nursing Mothers:

It is not known whether nitroglycerin is excreted in human milk. Because many drugs are excreted in human milk, caution should be exercised when nitroglycerin is administered to a nursing woman.

Pediatric Use:

Safety and effectiveness in pediatric patients have not been established.

Geriatric Use:

Clinical studies of NITRO-DUR Transdermal Infusion System did not include sufficient information to determine whether subjects 65 years and older respond differently from younger subjects. Additional clinical data from the published literature indicate that the elderly demonstrate increased sensitivity to nitrates, which may result in hypotension and increased risk of falling. In general, dose selection for an elderly patient should be cautious, usually starting at the low end of the dosing range, reflecting the greater frequency of the decreased hepatic, renal, or cardiac function, and of concomitant disease or other drug therapy.

ADVERSE REACTIONS

Adverse reactions to nitroglycerin are generally dose related, and almost all of these reactions are the result of nitroglycerins activity as a vasodilator. Headache, which may be severe, is the most commonly reported side effect. Headache may be recurrent with each daily dose, especially at higher doses. Transient episodes of lightheadedness, occasionally related to blood pressure changes, may also occur. Hypotension occurs infrequently, but in some patients it may be severe enough to warrant discontinuation of therapy. Syncope, crescendo angina, and rebound hypertension have been reported but are uncommon.

Allergic reactions to nitroglycerin are also uncommon, and the great majority of those reported have been cases of contact dermatitis or fixed drug eruptions in patients receiving nitroglycerin in ointments or patches. There have been a few reports of genuine anaphylactoid reactions, and these reactions can probably occur in patients receiving nitroglycerin by any route.

Extremely rarely, ordinary doses of organic nitrates have caused methemoglobinemia in normal-seeming patients. Methemoglobinemia is so infrequent at these doses that further discussion of its diagnosis and treatment is deferred (see OVERDOSAGE).

Application-site irritation may occur but is rarely severe.

In two placebo-controlled trials of intermittent therapy with nitroglycerin patches at 0.2 to 0.8 mg/hr, the most frequent adverse reactions among 307 subjects were as follows:

 | Placebo | Patch
Headache | 18% | 63%
Lightheadedness | 4% | 6%
Hypotension, and/or Syncope | 0% | 4%
Increased Angina | 2% | 2%

To report SUSPECTED ADVERSE REACTIONS, contact USPharma Ltd at 1(844)-750-3729 or FDA at 1-800-FDA-1088 or www.fda.gov/medwatch.

OVERDOSAGE

Hemodynamic Effects:

Nitroglycerin toxicity is generally mild. The estimated adult oral lethal dose of nitroglycerin is 200 mg to 1,200 mg. Infants may be more susceptible to toxicity from nitroglycerin. Consultation with a poison center should be considered.

Laboratory determinations of serum levels of nitroglycerin and its metabolites are not widely available, and such determinations have, in any event, no established role in the management of nitroglycerin overdose.

No data are available to suggest physiological maneuvers (eg, maneuvers to change the pH of the urine) that might accelerate elimination of nitroglycerin and its active metabolites. Similarly, it is not known which – if any – of these substances can usefully be removed from the body by hemodialysis.

No specific antagonist to the vasodilator effects of nitroglycerin is known, and no intervention has been subject to controlled study as a therapy of nitroglycerin overdose. Because the hypotension associated with nitroglycerin overdose is the result of venodilatation and arterial hypovolemia, prudent therapy in this situation should be directed toward increase in central fluid volume. Passive elevation of the patient’s legs may be sufficient, but intravenous infusion of normal saline or similar fluid may also be necessary.

The use of epinephrine or other arterial vasoconstrictors in this setting is likely to do more harm than good.

In patients with renal disease or congestive heart failure, therapy resulting in central volume expansion is not without hazard. Treatment of nitroglycerin overdose in these patients may be subtle and difficult, and invasive monitoring may be required.

Methemoglobinemia:

Nitrate ions liberated during metabolism of nitroglycerin can oxidize hemoglobin into methemoglobin. Even in patients totally without cytochrome b5 reductase activity, however, and even assuming that the nitrate moieties of nitroglycerin are quantitatively applied to oxidation of hemoglobin, about 1 mg/kg of nitroglycerin should be required before any of these patients manifests clinically significant (^310%) methemoglobinemia. In patients with normal reductase function, significant production of methemoglobin should require even larger doses of nitroglycerin. In one study in which 36 patients received 2 to 4 weeks of continuous nitroglycerin therapy at 3.1 to 4.4 mg/hr, the average methemoglobin level measured was 0.2%; this was comparable to that observed in parallel patients who received placebo.

Notwithstanding these observations, there are case reports of significant methemoglobinemia in association with moderate overdoses of organic nitrates. None of the affected patients had been thought to be unusually susceptible.

Methemoglobin levels are available from most clinical laboratories. The diagnosis should be suspected in patients who exhibit signs of impaired oxygen delivery despite adequate cardiac output and adequate arterial PO2. Classically, methemoglobinemic blood is described as chocolate brown, without color change on exposure to air.

Methemoglobinemia should be treated with methylene blue if the patient develops cardiac or CNS effects of hypoxia. The initial dose is 1 to 2 mg/kg infused intravenously over 5 minutes. Repeat methemoglobin levels should be obtained 30 minutes later and a repeat dose of 0.5 to 1.0 mg/kg may be used if the level remains elevated and the patient is still symptomatic. Relative contraindications for methylene blue include known NADH methemoglobin reductase deficiency or G-6-PD deficiency. Infants under the age of 4 months may not respond to methylene blue due to immature NADH methemoglobin reductase. Exchange transfusion has been used successfully in critically ill patients when methemoglobinemia is refractory to treatment.

DOSAGE AND ADMINISTRATION

The suggested starting dose is between 0.2 mg/hr* and 0.4 mg/hr*. Doses between 0.4 mg/hr* and 0.8 mg/hr* have shown continued effectiveness for 10 to 12 hours daily for at least 1 month (the longest period studied) of intermittent administration. Although the minimum nitrate-free interval has not been defined, data show that a nitrate-free interval of 10 to 12 hours is sufficient (see CLINICALPHARMACOLOGY). Thus, an appropriate dosing schedule for nitroglycerin patches would include a daily patch-on period of 12 to 14 hours and a daily patch-off period of 10 to 12 hours.

*Release rates were formerly described in terms of drug delivered per 24 hours. In these terms, the supplied NITRO-DUR systems would be rated at 2.5 mg/24 hours (0.1 mg/hour), 5 mg/24 hours (0.2 mg/hour), 7.5 mg/24 hours (0.3 mg/hour), 10 mg/24 hours (0.4 mg/hour), and 15 mg/24 hours (0.6 mg/hour).

Although some well-controlled clinical trials using exercise tolerance testing have shown maintenance of effectiveness when patches are worn continuously, the large majority of such controlled trials have shown the development of tolerance (ie, complete loss of effect) within the first 24 hours after therapy was initiated. Dose adjustment, even to levels much higher than generally used, did not restore efficacy.

HOW SUPPLIED

NITRO-DUR System Rated Release In Vivo* | Total nitroglycerin content | System size | Package Size
0.1 mg/hr | 20 mg | 5cm^2 | Unit Dose 30 (NDC 50742-513-01) Package 30 (NDC 50742-513-30)
0.2 mg/hr | 40 mg | 10 cm^2 | Unit Dose 30 (NDC 50742-514-01) Package 30 (NDC 50742-514-30)
0.3 mg/hr | 60 mg | 15 cm^2 | Unit Dose 30 (NDC 50742-515-01) Package 30 (NDC 50742-515-30)
0.4 mg/hr | 80 mg | 20 cm^2 | Unit Dose 30 (NDC 50742-516-01) Package 30 (NDC 50742-516-30)
0.6 mg/hr | 120 mg | 30 cm^2 | Unit Dose 30 (NDC 50742-517-01) Package 30 (NDC 50742-517-30)
0.8 mg/hr | 160 mg | 40 cm^2 | Unit Dose 30 (NDC 50742-518-01) Package 30 (NDC 50742-518-30)

*Release rates were formerly described in terms of drug delivered per 24 hours. In these terms, the supplied NITRO-DUR systems would be rated at 2.5 mg/24 hours (0.1 mg/hour), 5 mg/24 hours (0.2 mg/hour), 7.5 mg/24 hours (0.3 mg/hour), 10 mg/24 hours (0.4 mg/hour), and 15 mg/24 hours (0.6 mg/hour).

STORAGE AND HANDLING

Store at 25°C (77°F); excursions permitted to 15-30°C (59-86°F) [see USP Controlled Room Temperature]. Do not refrigerate.

Manufactured for:
Ingenus Pharmaceuticals, LLC
Orlando, FL 32839-6408
Revised: 07/2022
Rx only
51173205

Please read this instruction sheet carefully before using NITRO-DUR

Information for the Patient About—
Nitro-Dur®
(nitroglycerin)
Transdermal Infusion System

Summary
NITRO-DUR® is a unique method of administering nitroglycerin to the bloodstream. NITRO-DUR eliminates the swallowing of pills or the application of a messy ointment. Nitroglycerin is a medication your doctor has prescribed for you to help reduce the frequency and severity of angina attacks (chest pain).

How your NITRO-DUR Transdermal Infusion System works
Nitroglycerin causes the veins (vessels that return blood to the heart) to relax so that the work load of the heart is reduced. This lowers the heart's oxygen needs.

As a result, the heart muscle is well nourished and the frequency of angina attacks is reduced. NITRO-DUR is applied directly to the skin. The nitroglycerin passes from the adhesive surface through the skin—allowing medication to be absorbed directly into the bloodstream. This manner of delivering medicine to your bloodstream provides you with nitroglycerin with one daily application of a NITRO-DUR unit.

Instructions for use

Placement area
Select a reasonably hair-free application site. Avoid extremities below the knee or elbow, skin folds, scar tissue, burned or irritated areas.

Application
Wash hands before applying.

Hold the unit with brown lines facing you, in an up and down position.

Bend the sides of unit away from you, then toward you until you hear the "SNAP".

Peel off one side of the plastic backing.

Using the other half of the backing as a handle, apply the sticky side of the patch to the skin.

Press the sticky side on the skin, and smooth down.

Fold back the remaining side of the patch. Grasp the edge of the plastic applicator by the stripe, and pull it across the skin.

Wash hands to remove any drug.

Removal

Press down on the center of the system to raise its outer edge away from the skin.

Grasp the edge gently, and slowly peel the unit away from skin.
Wash skin area with soap and water. Towel dry. Wash hands. You may use a different application site every
day.

Skin care

1. After you remove NITRO-DUR, your skin may feel warm and appear red. This is normal. The redness will disappear in a short time. If the area feels dry, you may apply a soothing lotion.
2. Any redness or rash that does not disappear should be called to your doctor's attention.

Cautions
If your doctor has prescribed "under-the-tongue" nitroglycerin tablets in addition to NITRO-DUR, you should sit down before taking the "under-the-tongue" tablet. If dizziness should occur, notify your doctor. This may be an indication that the "under-the-tongue" tablet dosage needs to be reduced.

Possible side effects
The most common side effect experienced by people taking nitroglycerin is headache. Your doctor may tell you to take a mild analgesic to relieve the headache.

Some people may experience dizziness. This is due to a slight decrease in blood pressure, which is usually experienced when a person changes position, from lying flat to sitting upright or from sitting to standing. If this occurs, sit down until the dizziness stops, then notify your doctor.

He or she may wish to reduce your NITRO-DUR dosage. In some people, nitroglycerin preparations may cause the skin to feel flushed or the heart to beat faster. If this should occur, notify your doctor; again, he or she may wish to change your NITRO-DUR dosage.

NITRO-DUR is a unique drug that depends on direct contact with the skin to work. For this reason, the skin should be reasonably hair-free, clean, and dry.

Other information

1. Allow NITRO-DUR to stay in place as directed by your doctor.
2. Showering is permitted with NITRO-DUR in place.
3. NITRO-DUR should be kept out of reach of children and pets.
4. Store at room temperature 77°F (25°C).
5. NITRO-DUR is boxed so that you have a 30-day supply. Be sure to check your supply periodically. Before it runs low, you should visit your pharmacist for a refill or ask your doctor to renew your NITRO-DUR prescription.
6. It is important that you do not miss a day of your NITRO-DUR therapy. If your schedule needs to be changed, your doctor will give you special instructions.
7. NITRO-DUR has been prescribed for you. Do not give your medication to anyone else.
8. NITRO-DUR is for prevention of angina; not for treatment of an acute angina attack.
9. Notify your doctor if angina attacks change for the worse.

BOXED WARNING

You must consult your doctor for important information before using this drug.

Manufactured for:
Ingenus Pharmaceuticals, LLC
Orlando, FL 32839-6408

Revised: 09/2017

18143949

PRINCIPAL DISPLAY PANEL - 20 mg Pouch Box

NDC 50742-513-30
Contents: 30 units
Nitro-Dur®
(nitroglycerin)
Transdermal Infusion System
0.1 mg/hr (5 cm^2)
Each unit contains 20 mg of
nitroglycerin in acrylic-based
polymer adhesives with a
resinous cross-linking agent.
Rated release in vivo 0.1 mg/hr.
Rx only

PRINCIPAL DISPLAY PANEL - 40 mg Pouch Box

NDC 50742-514-30
Contents: 30 units
Nitro-Dur®
(nitroglycerin)
Transdermal Infusion System
0.2 mg/hr (10 cm2)
Each unit contains 40 mg of
nitroglycerin in acrylic-based
polymer adhesives with a
resinous cross-linking agent.
Rated release in vivo 0.2 mg/hr.
Rx only

PRINCIPAL DISPLAY PANEL - 60 mg Pouch Box

NDC 50742-515-30
Contents: 30 units
Nitro-Dur®
(nitroglycerin)
Transdermal Infusion System
0.3 mg/hr (15 cm^2)
Each unit contains 60 mg of
nitroglycerin in acrylic-based
polymer adhesives with a
resinous cross-linking agent.
Rated release in vivo 0.3 mg/hr.
Rx only

PRINCIPAL DISPLAY PANEL - 80 mg Pouch Box

NDC 50742-516-30
Contents: 30 units
Nitro-Dur®
(nitroglycerin)
Transdermal Infusion System
0.4 mg/hr (20 cm^2)
Each unit contains 80 mg of
nitroglycerin in acrylic-based
polymer adhesives with a
resinous cross-linking agent.
Rated release in vivo 0.4 mg/hr.
Rx only

PRINCIPAL DISPLAY PANEL - 120 mg Pouch Box

NDC 50742-517-30
Contents: 30 units
Nitro-Dur®
(nitroglycerin)
Transdermal Infusion System
0.6 mg/hr (30 cm^2)
Each unit contains 120 mg of
nitroglycerin in acrylic-based
polymer adhesives with a
resinous cross-linking agent.
Rated release in vivo 0.6 mg/hr.
Rx only

PRINCIPAL DISPLAY PANEL - 160 mg Pouch Box

NDC 50742-518-30
Contents: 30 units
Nitro-Dur®
(nitroglycerin)
Transdermal Infusion System
0.8 mg/hr (40 cm^2)
Each unit contains 160 mg of
nitroglycerin in acrylic-based
polymer adhesives with a
resinous cross-linking agent.
Rated release in vivo 0.8 mg/hr.
Rx only